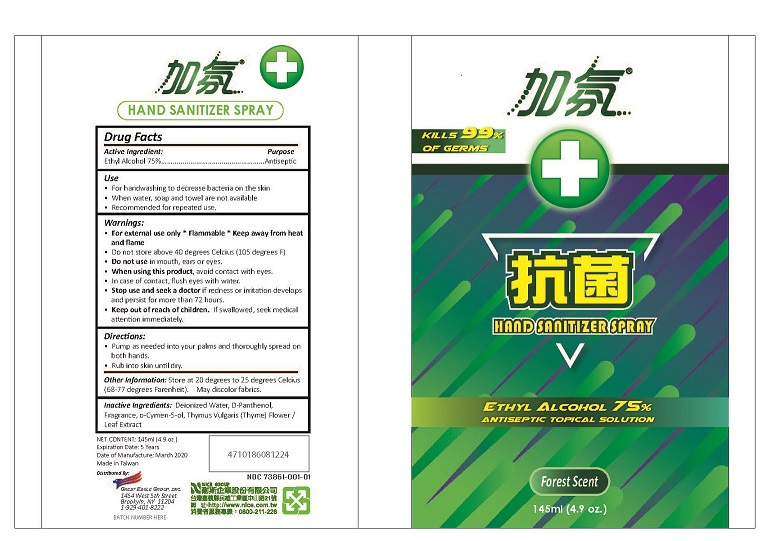 DRUG LABEL: Hand Sanitizer FOREST SCENT
NDC: 73861-001 | Form: SPRAY
Manufacturer: GREAT EAGLE GROUP INC
Category: otc | Type: HUMAN OTC DRUG LABEL
Date: 20200327

ACTIVE INGREDIENTS: ALCOHOL 750 mg/1 mL
INACTIVE INGREDIENTS: O-CYMEN-5-OL; WATER; PANTHENOL; THYME

Hand Sanitizer FOREST SCENT

Active lngredient

ETHYL ALCOHOL

Purpose

Antiseptic

Uses

Hand sanitizer to help reduce bacteria that potentially can cause disease. For use when soap and water are not available.

Recomended for repeated use.

Warnings

- For external use only
- Flammable
- Keep away from heat and flame.
- Do not use in ear , mouth OR eyes.
- When using this product

Avoid contact with eyes. In case of eye contact, flush with water.

- Keep out of reachof children.

If swallowed, seek medical attention immidately.

Directions

Pump as needed in to your palms and throughly spread on both hand.

Rub into skin until dry.

Inactives

Deionized Water,
D-Panthenol
Fragrance
o-Cymen-5-ol
Thymus Vulgaris (Thyme) Flower/Leaf Extract

KEEP OUT OF REACH OF CHILDREN